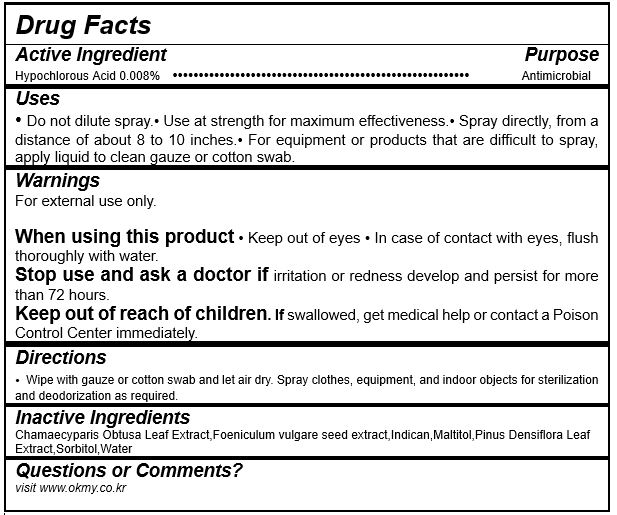 DRUG LABEL: JIKIMI Phytoncide
NDC: 71544-0020 | Form: LIQUID
Manufacturer: MY Corp.,Ltd
Category: otc | Type: HUMAN OTC DRUG LABEL
Date: 20201113

ACTIVE INGREDIENTS: HYPOCHLOROUS ACID 0.00136 g/17 mL
INACTIVE INGREDIENTS: CHAMAECYPARIS OBTUSA LEAF; INDICAN; MALTITOL; PINUS DENSIFLORA LEAF; SORBITOL; WATER

MY Corp - JIKIMI Phytoncide

ACTIVE INGREDIENT

Hypochlorous Acid

INACTIVE INGREDIENT

Chamaecyparis Obtusa Leaf Extract, Foeniculum vulgare seed extract, Indican, Maltitol, Pinus Densiflora Leaf Extract, Sorbitol, Water

PURPOSE

- Do not dilute spray.
- Use at strength for maximum effectiveness.
- Spray directly, from a distance of about 8 to 10 inches.
- For equipment or products that are difficult to spray, apply liquid to clean gauze or cotton swab.

keep out of reach of the children

INDICATIONS AND USAGE

Wipe with gauze or cotton swab and let air dry. Spray clothes, equipment, and indoor objects for sterilization and deodorization as required.

WARNINGS

For external use only.

When using this product

- Keep out of eyes
- In case of contact with eyes, flush thoroughly with water.

Stop use and ask a doctor if irritation or redness develop and persist for more than 72 hours.

Keep out of reach of children. If swallowed, get medical help or contact a Poison Control Center immediately.

DOSAGE AND ADMINISTRATION

for external use only